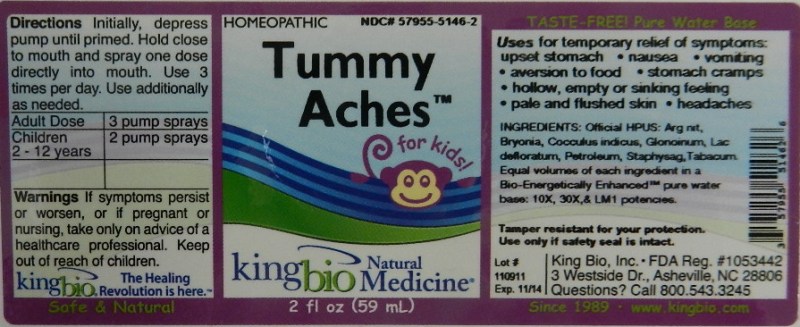 DRUG LABEL: Tummy Aches
NDC: 57955-5146 | Form: LIQUID
Manufacturer: King Bio Inc.
Category: homeopathic | Type: HUMAN OTC DRUG LABEL
Date: 20111222

ACTIVE INGREDIENTS: SILVER NITRATE 10 [hp_X]/59 mL; BRYONIA ALBA ROOT 10 [hp_X]/59 mL; ANAMIRTA COCCULUS SEED 10 [hp_X]/59 mL; NITROGLYCERIN 10 [hp_X]/59 mL; SKIM MILK 10 [hp_X]/59 mL; KEROSENE 10 [hp_X]/59 mL; DELPHINIUM STAPHISAGRIA SEED 10 mL/59 mL; TOBACCO LEAF 10 [hp_X]/59 mL
INACTIVE INGREDIENTS: WATER

Tummy Aches

Active Ingredient's

Official HPUS: Argentum Nitricum, Bryonia, Cocculus Indicus, Glonoinum, Lac Defloratum, Petroleum, Staphysagria and Tabacum.

Reference image tummy.jpg

Inactive Ingredient

Equal volumes of each ingredient in a Bio-Energetically Enhanced pure water base: 10X, 30X, and LM1 potencies.

Reference image tummy.jpg

Indications and Usage

Uses for temporary relief of symptoms:

- upset stomach
- nausea
- vomiting
- aversion to food
- stomach cramps
- hollow, empty or sinking feeling
- pale and flushed skin
- headaches

Reference image tummy.jpg

Dosage and Administration

Directions Initially, depress pump until primed. Hold close to mouth and spray one dose directly into mouth. Use 3 times per day. Use additionally as needed.

Adult Dose 3 pump sprays

Children 2-12 years 2 pump sprays

Reference image tummy.jpg

Warnings

If symptoms persist or worsen, or if pregnant or nursing, take only on advice of a healthcare professional.

Other: Tamper resistant for your protection. Use only if safety seal is intact.

Reference image tummy.jpg

Keep out of reach of children.

Reference image tummy.jpg

Purpose

Uses for temporary relief of symptoms: upset stomach, nausea, vomiting, aversion to food, stomach cramps, hollow, empty or sinking feeling, pale and flushed skin and headaches.

Reference image tummy.jpg

PACKAGE LABEL

King Bio Inc,

3 Westside Drive

Asheville, NC 28806

Questions? Call 800.543.3245

www.kingbio.com

Homeopathic

Safe and Natural